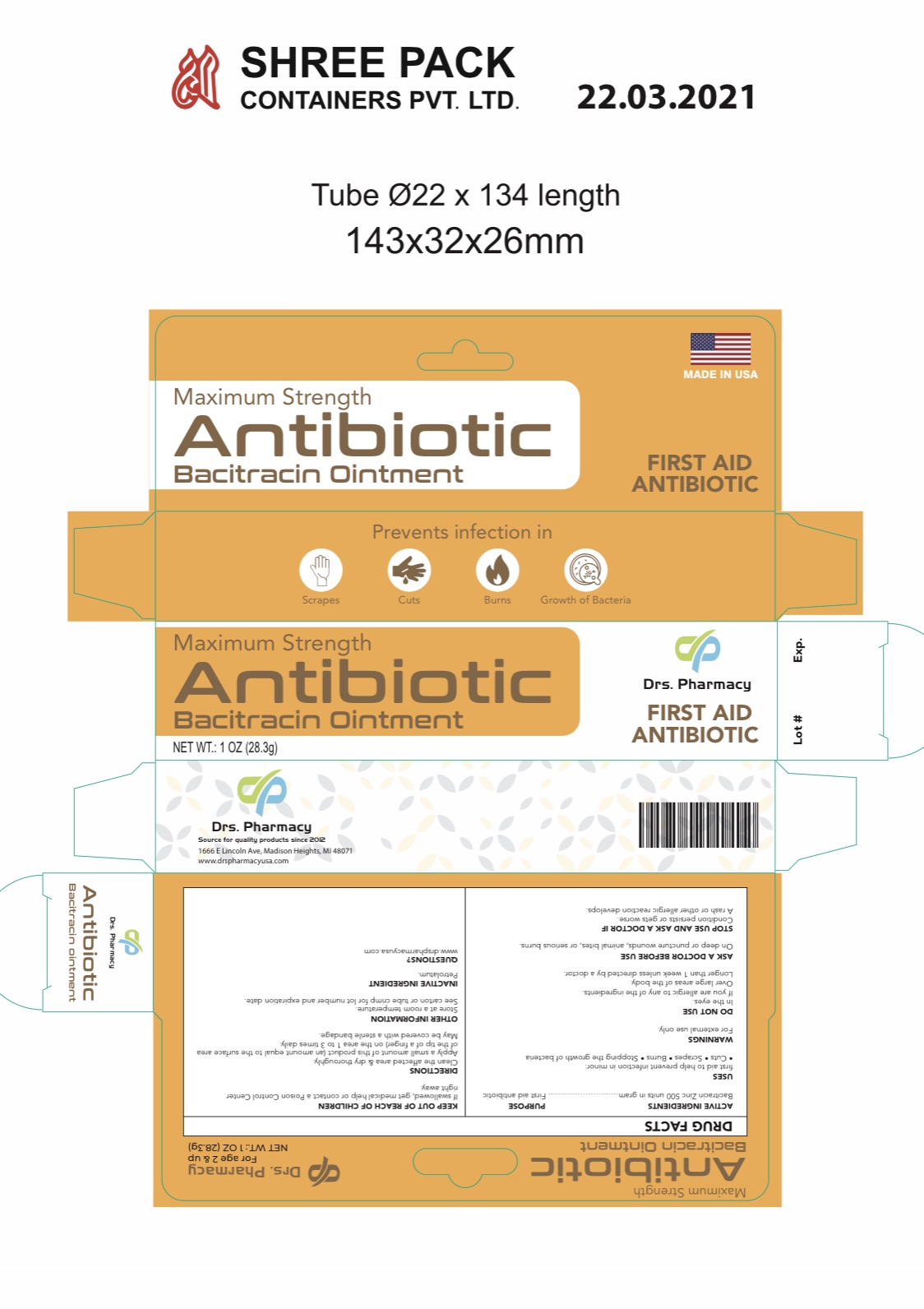 DRUG LABEL: Drs.  Antibiotic Bacitracin
NDC: 80489-006 | Form: OINTMENT
Manufacturer: OL PHARMA TECH, LLC
Category: otc | Type: HUMAN OTC DRUG LABEL
Date: 20250109

ACTIVE INGREDIENTS: BACITRACIN ZINC 500 [USP'U]/1 g
INACTIVE INGREDIENTS: PETROLATUM

Active ingredient

Bacitracin zinc 500 units in one gram

Purpose

First aid antibiotic

Uses

First aid to help prevent infection in :

- minor cuts
- burns
- scrapes

Warnings

For external use only.

Do not use

• if you are allergic to any of the ingredients
• in the eyes
• over large areas of the body
• longer than 1 week unless directed by a doctor

Ask a doctor before use

on deep or puncture wounds, animal bites, or serious burns

Stop use

Stop use and ask a doctor if

- condition persists or gets worse
- a rash or other allergic reaction develops

Directions

- clean the affected area and dry thoroughly
- apply a small amount of this product (an amount equal to the surface area of the tip of a finger) on the area 1 to 3 times daily
- may be covered with a sterile bandage

Storage and Handling

- store at room temperature
- see carton or tube crimp for lot number and expiration date

Inactive ingredient

Petrolatum

keep out of reach of children

If swallowed get medical help or contact a poison control center right away

Questions

www.drspharmacyusa.com

PACKAGE LABEL

Drs. Bacitracin Antibiotic ointment